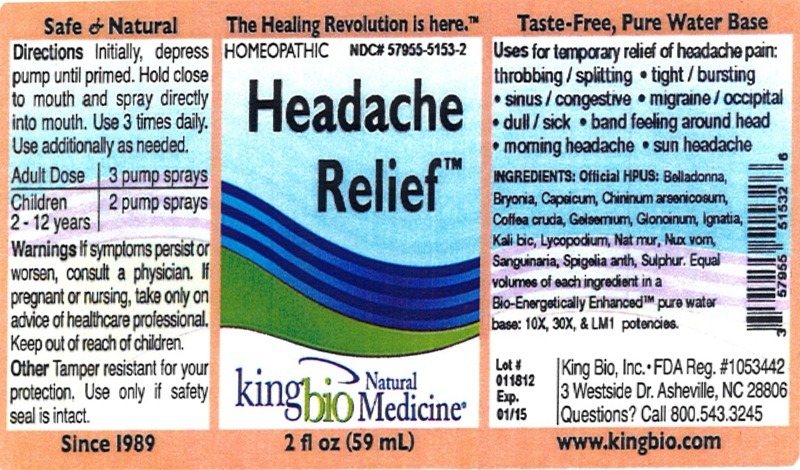 DRUG LABEL: Headache Relief
NDC: 57955-5153 | Form: SPRAY
Manufacturer: King Bio Inc.
Category: homeopathic | Type: HUMAN OTC DRUG LABEL
Date: 20120402

ACTIVE INGREDIENTS: ATROPA BELLADONNA 10 [hp_X]/59 mL; BRYONIA ALBA ROOT 10 [hp_X]/59 mL; CAPSICUM 10 [hp_X]/59 mL; QUININE ARSENITE 10 [hp_X]/59 mL; ARABICA COFFEE BEAN 10 [hp_X]/59 mL; GELSEMIUM SEMPERVIRENS ROOT 10 [hp_X]/59 mL; NITROGLYCERIN 10 [hp_X]/59 mL; STRYCHNOS IGNATII SEED 10 [hp_X]/59 mL; POTASSIUM DICHROMATE 10 [hp_X]/59 mL; LYCOPODIUM CLAVATUM SPORE 10 [hp_X]/59 mL; SODIUM CHLORIDE 10 [hp_X]/59 mL; STRYCHNOS NUX-VOMICA SEED 10 [hp_X]/59 mL; SANGUINARIA CANADENSIS ROOT 10 [hp_X]/59 mL; SPIGELIA ANTHELMIA 10 [hp_X]/59 mL; SULFUR 10 [hp_X]/59 mL
INACTIVE INGREDIENTS: WATER

Headache Relief

Active Ingredients

Official HPUS: Belladonna, Bryonia, Capsicum annuum, Chininum arsenicosum, Coffea cruda, Gelsemium sempervirens, Glonoinum, Ignatia amara, Kali bichromicum, Lycopodium clavatum, Natrum muriaticum, Nux vomica, Sanguinaria canadensis, Spigelia anthelmia, Sulphur.

Reference image headacherelief.jpg

Warnings

If symptoms persist or worsen, consult a physician. If pregnant or nursing, take only on advice of healthcare professional. Keep out of reach of children.

Other: Tamper resistant for your protection. Use only if safety seal is intact.

Reference image headacherelief.jpg

Purposes

Uses for temporary relief of headache pain:

- throbbing / splitting
- tight / bursting
- sinus / congestive
- migraine / occipital
- dull / sick
- band feeling around head
- morning headache
- sun headache

Reference image headacherelief.jpg

Indications and Usage

Uses for temporary relief of headache pain: throbbing/splitting, tight/bursting, sinus/congestive, migraine/occipital, dull/sick, band feeling around head, morning headache, sun headache

Reference image headacherelief.jpg

Keep out of reach of children.

Reference image headacherelief.jpg

Dosage and Administration

Directions: Initially, depress pump until primed. Hold close to mouth and spray directly into mouth. Use 3 times daily. Use additionally as needed.

Adult Dose - 3 pump sprays

Children (2-12 years) - 2 pump sprays

Reference image headacherelief.jpg

Inactive Ingredients

Equal volumes of each ingredient in a Bio-Energetically Enhanced pure water base: 10X, 30X, and LM1 potencies.

Reference image headacherelief.jpg

PACKAGE LABEL

King Bio, Inc.

3 Westside Dr

Asheville, NC 28806

Questions? Call 800.543.3245

www.kingbio.com